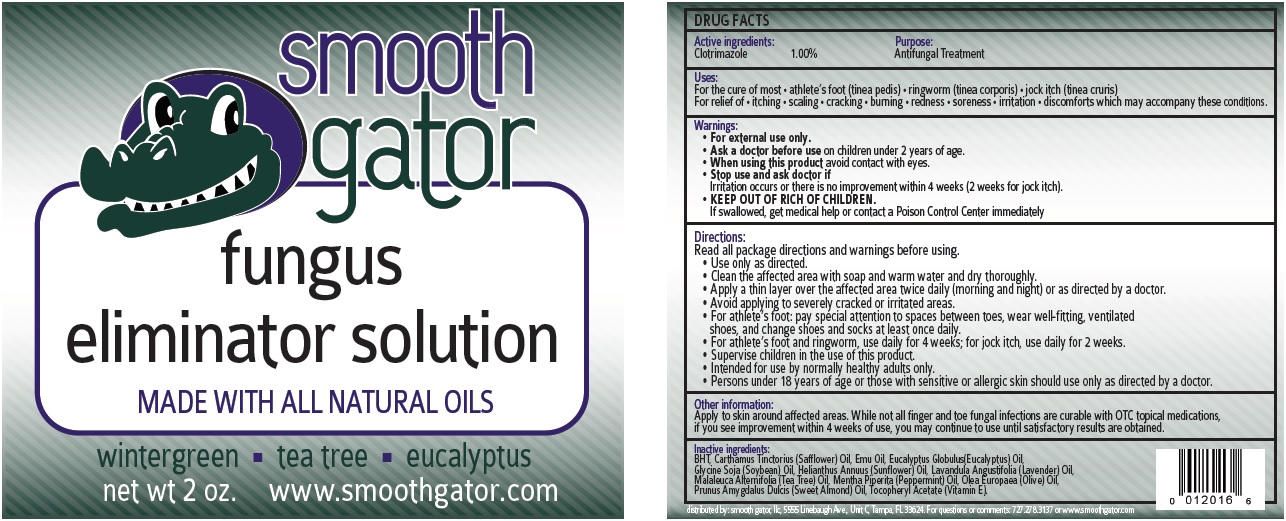 DRUG LABEL: Smooth Gator Fungus Eliminator
NDC: 70673-747 | Form: LIQUID
Manufacturer: Smooth Gator, LLC
Category: otc | Type: HUMAN OTC DRUG LABEL
Date: 20231110

ACTIVE INGREDIENTS: CLOTRIMAZOLE 10 mg/1 mL
INACTIVE INGREDIENTS: BUTYLATED HYDROXYTOLUENE; SAFFLOWER; EMU OIL; EUCALYPTUS OIL; SOYBEAN OIL; HELIANTHUS ANNUUS FLOWERING TOP; LAVENDER OIL; TEA TREE OIL; PEPPERMINT OIL; OLEA EUROPAEA (OLIVE) OIL UNSAPONIFIABLES; ALMOND OIL; .ALPHA.-TOCOPHEROL ACETATE

Smooth Gator Fungus Eliminator Solution

Active ingredients:

Clotrimazole 1.00%

Purpose:

Antifungal Treatment

Uses:

For the cure of most • athlete’s foot (tinea pedis) • ringworm (tinea corporis) • jock itch (tinea cruris) For relief of • itching • scaling • cracking • burning • redness • soreness • irritation • discomforts which may accompany these conditions.

Warnings:

- For external use only.

Ask a doctor before use

- on children under 2 years of age.

When using this product

- avoid contact with eyes.

Stop use and ask doctor if

Irritation occurs or there is no improvement within 4 weeks (2 weeks for jock itch).

KEEP OUT OF RICH OF CHILDREN.

If swallowed, get medical help or contact a Poison Control Center immediately

Directions:

Read all package directions and warnings before using. • Use only as directed. • Clean the affected area with soap and warm water and dry thoroughly. • Apply a thin layer over the affected area twice daily (morning and night) or as directed by a doctor. • Avoid applying to severely cracked or irritated areas. • For athlete’s foot: pay special attention to spaces between toes, wear well-fitting, ventilated shoes, and change shoes and socks at least once daily. • For athlete’s foot and ringworm, use daily for 4 weeks; for jock itch, use daily for 2 weeks. • Supervise children in the use of this product. • Intended for use by normally healthy adults only. • Persons under 18 years of age or those with sensitive or allergic skin should use only as directed by a doctor.

Other information:

Apply to skin around affected areas. While not all finger and toe fungal infections are curable with OTC topical medications, if you see improvement within 4 weeks of use, you may continue to use until satisfactory results are obtained.

Inactive ingredients:

BHT, Carthamus Tinctorius (Safflower) Oil, Emu Oil, Eucalyptus Globulus(Eucalyptus) Oil, Glycine Soja (Soybean) Oil, Helianthus Annuus (Sunflower) Oil, Lavandula Angustifolia (Lavender) Oil, Malaleuca Alternifolia (Tea Tree) Oil, Mentha Piperita (Peppermint) Oil, Olea Europaea (Olive) Oil, Prunus Amygdalus Dulcis (Sweet Almond) Oil, Tocopheryl Acetate (Vitamin E).